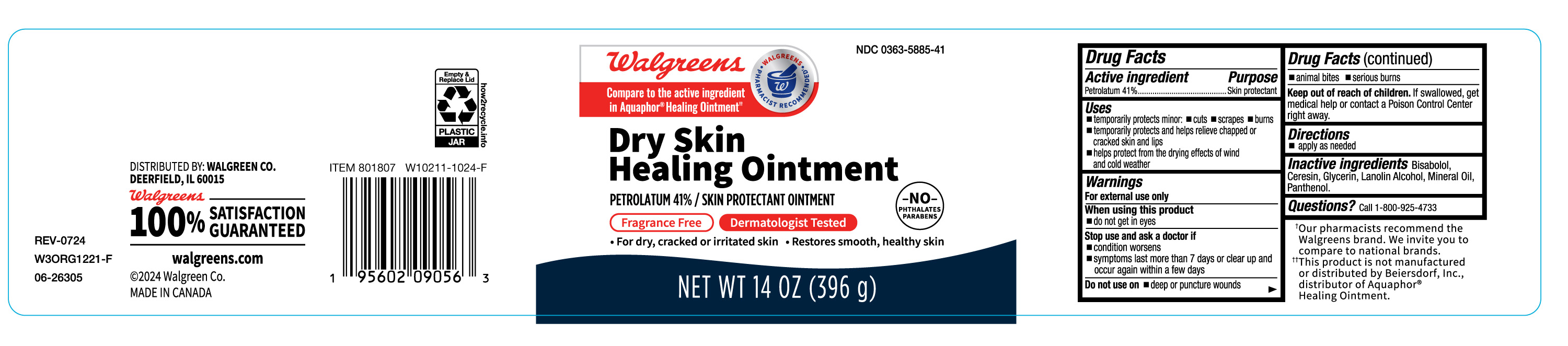 DRUG LABEL: Dry Skin Healing
NDC: 0363-5885 | Form: LOTION
Manufacturer: Walgreen
Category: otc | Type: HUMAN OTC DRUG LABEL
Date: 20241105

ACTIVE INGREDIENTS: PETROLATUM 41 g/100 g
INACTIVE INGREDIENTS: CERESIN; MINERAL OIL; PANTHENOL; GLYCERIN; .ALPHA.-BISABOLOL, (+)-; LANOLIN ALCOHOLS

Dry skin, Healing Ointment, NDC-0363-5885-41

Active Ingredient

Petrolatum 41%

Purpose

Skin protectant

Uses

- temporarily protects minor: cuts, scrapes, burns.
- temporarily protects and helps relieve chapped or cracked skin and lips.
- helps protect from the drying effects of wind and cold weather.

Warnings

For external use only

When using this product

- Do not get in eyes.

Stop use and ask a doctor if

- condition worsens
- symptoms last more than 7 days or clear up and occur within a few days.

Do not use on

- Deep or puncture wounds
- animal bites.
- serious burns

Keep out of reach of children

If swallowed, get medical help or contact a Poison Control Center right away.

Directions

- Apply as needed.

Inactive Ingredients

Mineral Oil, Ceresin, Lanolin Alcohol, Panthenol, Glycerin, Bisabolol.

Questions?

Call 1-800-925-4733